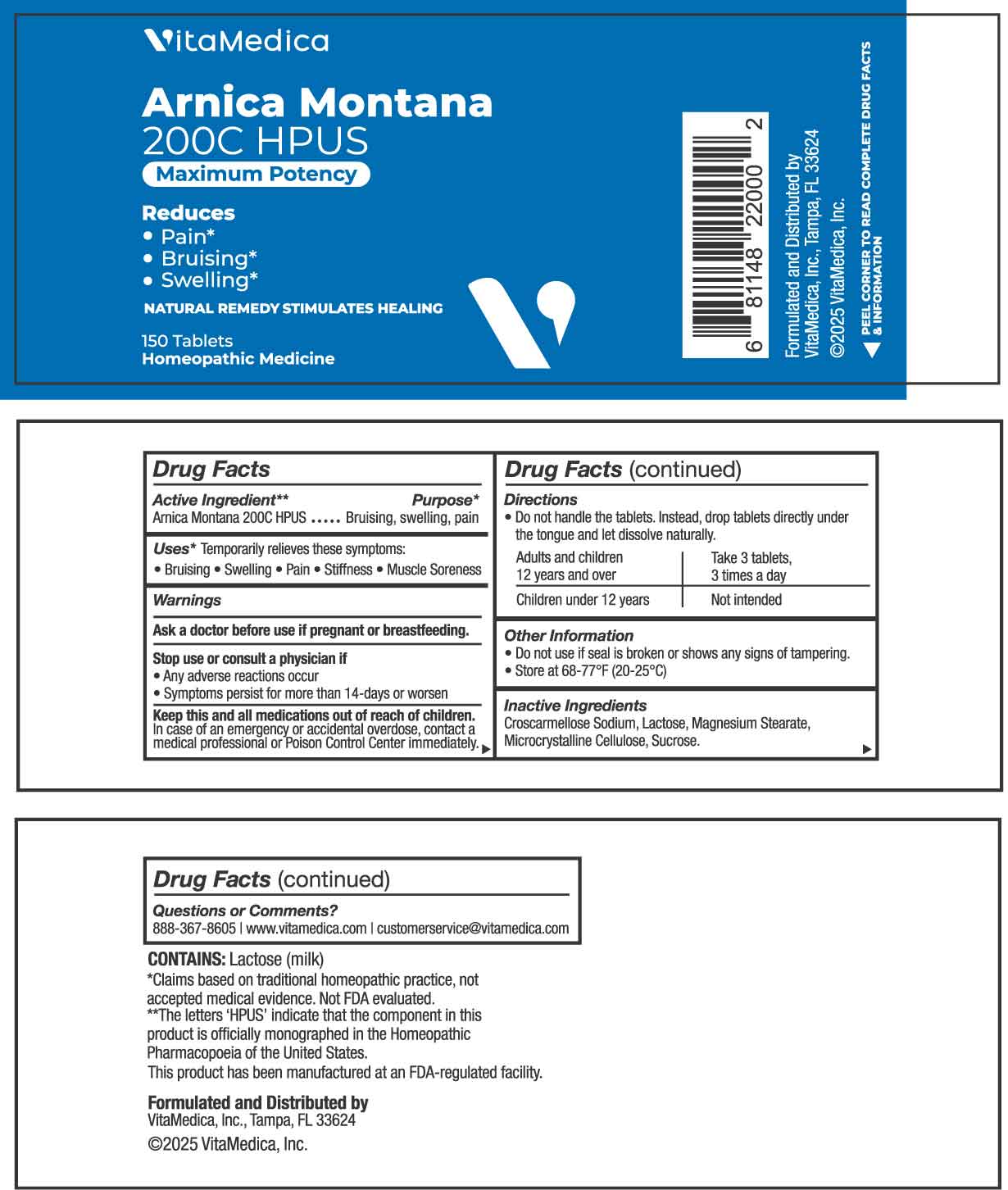 DRUG LABEL: Arnica Montana 200C HPUS
NDC: 80004-009 | Form: TABLET
Manufacturer: VITAMEDICA, INC.
Category: homeopathic | Type: HUMAN OTC DRUG LABEL
Date: 20260123

ACTIVE INGREDIENTS: ARNICA MONTANA WHOLE 200 [hp_C]/1 1
INACTIVE INGREDIENTS: CROSCARMELLOSE; LACTOSE MONOHYDRATE; MAGNESIUM STEARATE; MICROCRYSTALLINE CELLULOSE; SUCROSE

DRUG FACTS:

ACTIVE INGREDIENT:

Arnica Montana 200C HPUS.**

**The letters 'HPUS' indicate that the component in this product is officially monographed in the Homeopathic Pharmacopoeia of the United States. This product has been manufactured at an FDA-regulated facility.

PURPOSE:

Arnica Montana - Bruising, swelling, pain*

*Claims based on traditional homeopathic practice, not accepted medical evidence. Not FDA evaluated.

USES:

*Temporarily relieves these symptoms:

• Bruising • Swelling • Pain • Stiffness • Muscle Soreness

*Claims based on traditional homeopathic practice, not accepted medical evidence. Not FDA evaluated.

WARNINGS:

Ask a doctor before use if pregnant or breastfeeding.

Stop use or consult a physician if

• Any adverse reactions occur

• Symptoms persist for more than 14-days or worsen

Keep this and all medications out of reach of children.

In case of an emergency or accidental overdose, contact a medical professional or Poison Control immediately.

CONTAINS: Lactose (milk)

• Do not use if seal is broken or shows any signs of tampering.

• Store at 68-77°F (20-25°C)

KEEP OUT OF REACH OF CHILDREN:

In case of an emergency or accidental overdose, contact a medical professional or Poison Control immediately.

DIRECTIONS:

• Do not handle the tablets. Instead, drop tablets directly under the tongue and let dissolve naturally.

Adults and children 12 years and over - Take 3 tablets, 3 times a day

Children under 12 years - Not intended

INACTIVE INGREDIENTS:

Croscarmellose Sodium, Lactose, Magnesium Stearate, Microcrystalline Cellulose, Sucrose.

QUESTIONS:

Formulated and Distributed by

VitaMedica, Inc.

Tampa, Fl 33624

©2025 VitaMedica, Inc.

888-367-8605

www.vitamedica.com

customerservice@vitamedica.com

PACKAGE DISPLAY LABEL

VitaMedica

Arnica Montana

200C HPUS

Maximum Potency

Reduces

•Pain*

•Bruising*

•Swelling*

Natural Remedy Stimulates Healing

150 Tablets

Homeopathic Medicine